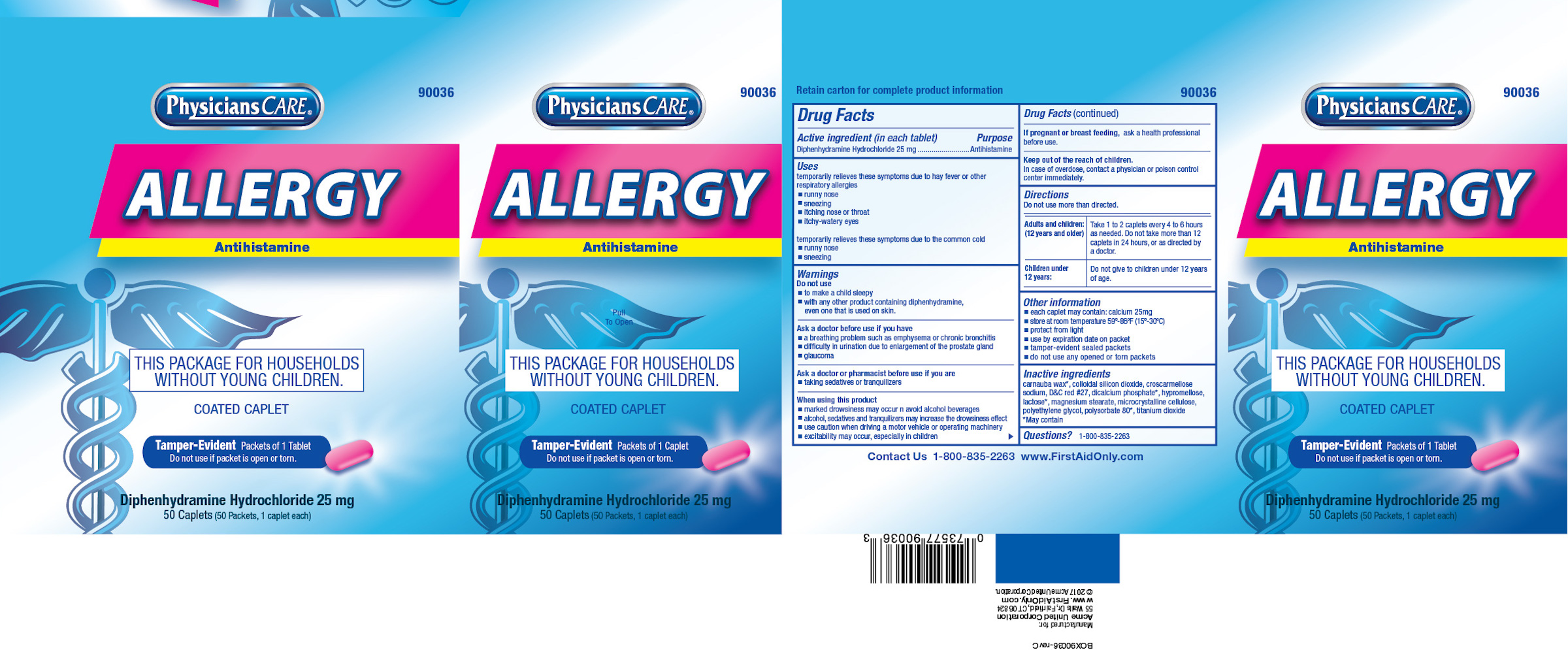 DRUG LABEL: PhysiciansCare Allergy
NDC: 0924-0056 | Form: TABLET, FILM COATED
Manufacturer: Acme United Corporation
Category: otc | Type: HUMAN OTC DRUG LABEL
Date: 20241109

ACTIVE INGREDIENTS: DIPHENHYDRAMINE HYDROCHLORIDE 25 mg/1 1
INACTIVE INGREDIENTS: CELLULOSE, MICROCRYSTALLINE; CARNAUBA WAX; POLYETHYLENE GLYCOL 2000; SILICON DIOXIDE; CROSCARMELLOSE SODIUM; TITANIUM DIOXIDE; MAGNESIUM STEARATE; ANHYDROUS DIBASIC CALCIUM PHOSPHATE; HYPROMELLOSE 2208 (100 MPA.S); ANHYDROUS LACTOSE; POLYSORBATE 80; D&C RED NO. 27

PhysiciansCare Allergy

Active Ingredients (in each tablet)

Diphenhydramine Hydochloride 25 mg

Purpose

Antihistamine

Uses
temporarily relieves these symptoms due to hay fever or other respiratory allergies

- runny nose
- sneezing
- itching nose or throat
- itchy-watery eyes

temporarily relieves these symptoms due to the common cold

- runny nose
- sneezing

Warnings

Do Not Use

- to make a child sleepy
- with any other product containing diphenhydramine, even one that is used on the skin.

Ask a doctor before use if you have

- a breathing problem such as emphysema or chronic bronchitis
- difficuly in urination due to enlargement of the prostate gland
- glaucoma

Ask a doctor or pharmacist before use if you are

- taking sedatives or tranquilizers

When using this product
* marked drowsiness may occur and avoid alcoholic beverages
* alcohol, sedatives and tranquilizers may increase the drowsiness effect
* use caution when driving a motor vehicle or operating machinery
* excitability may occur, especially in children

If pregnant or breast feeding, ask a health professional

before use

Keep out of the reach of children.

In case of overdose, contact a physician or poison control center immediately.

Directions

Do not use more than directed

Adults and children: (12 years and older)

Take 1 to 2 caplets every 4 to 6 hours as needed. Do not take more than 12 caplets in 24 hours, or as directed by a doctor.

Children under 12 years:

Do not give to children under 12 years of age.

Other information

- each caplet may contain: calium 25mg
- store at room temperature 59°-86°F (15°-30°C)
- protect from light
- use by expiration date on packet
- tamper-evident sealed packets
- do not use any opened or torn packets

Inactive ingredients

carnauba wax*, colloidal silicon dioxide, croscarmellose sodium, D&C red #27, dicalcium phosphate, hypromellose, lactose, magnesium stearate, microcrystalline cellulose, polyethylene glycol, polysorbate 80*, titanium dioxide
*may contain.

Questions?

1-800-835-2263

PACKAGE LABEL

BOX16790056-revC.jpg

PACKAGE LABEL

Box18490036-revC.jpg